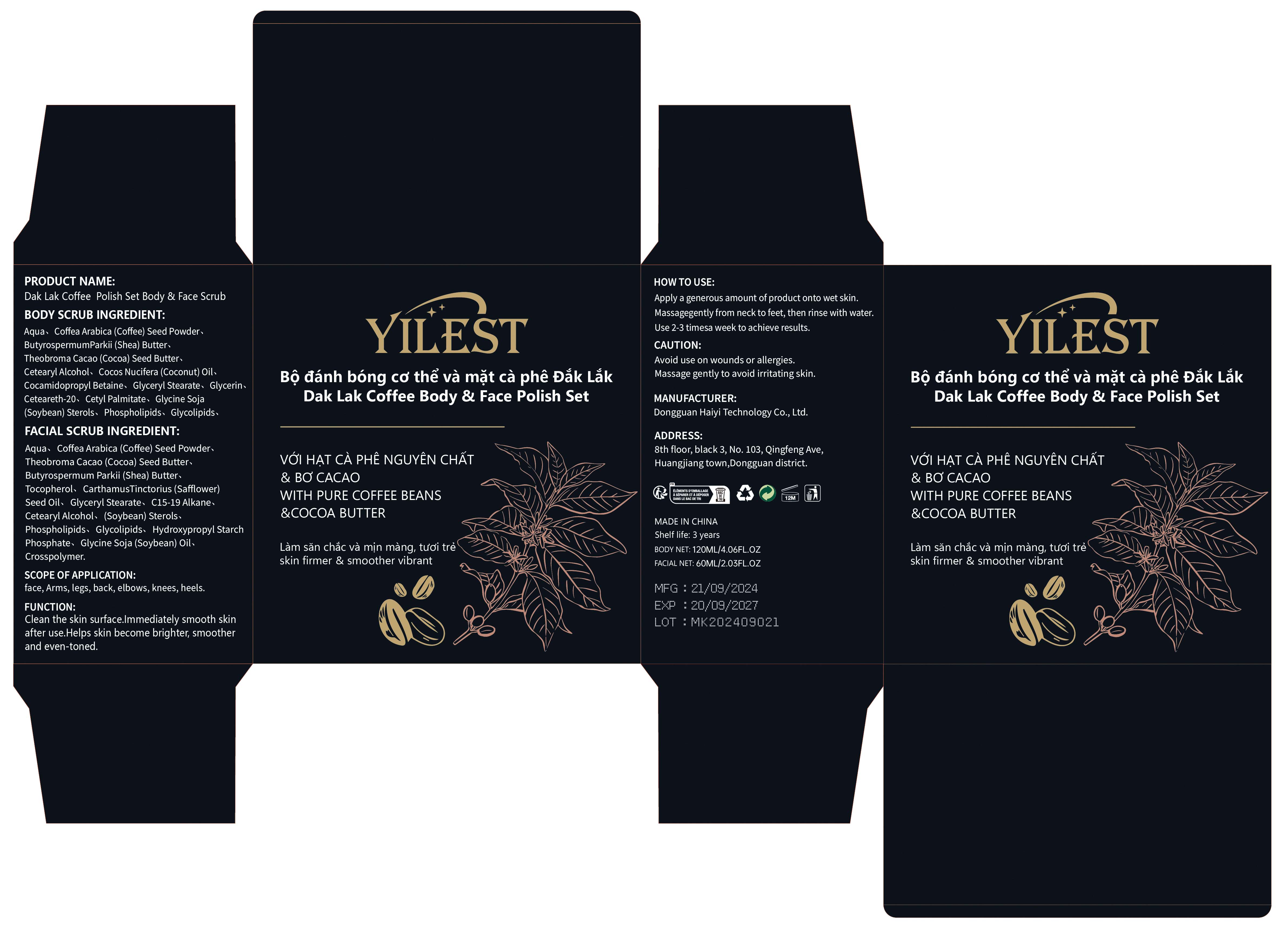 DRUG LABEL: Dak Lak Coffee Polish Set Body  Face scrub
NDC: 84732-083 | Form: PASTE
Manufacturer: Dongguan Haiyi Technology Co.,Ltd.
Category: otc | Type: HUMAN OTC DRUG LABEL
Date: 20241105

ACTIVE INGREDIENTS: CETEARYL ALCOHOL 1 mg/100 mL
INACTIVE INGREDIENTS: WATER; GLYCERIN; CETYL PALMITATE; GLYCINE SOJA (SOYBEAN) STEROLS; EGG PHOSPHOLIPIDS; TOCOPHEROL; BUTYROSPERMUM PARKII (SHEA) BUTTER; COCAMIDOPROPYL BETAINE; C15-19 ALKANE; THEOBROMA CACAO (COCOA) SEED BUTTER; COCOS NUCIFERA (COCONUT) OIL; CARTHAMUS TINCTORIUS (SAFFLOWER) SEED OIL; CETEARETH-20; COFFEA ARABICA (COFFEE) SEED EXTRACT; GLYCERYL STEARATE

Active ingredient

Cetearyl Alcohol

Inactive ingredient

BODY SCRUB INGREDIENT:

Aqua、Coffea Arabica (Coffee) Seed Powder、ButyrospermumParkii (Shea) Butter、Theobroma Cacao (Cocoa) Seed Butter、Cocos Nucifera (Coconut) Oil,Cocamidopropyl Betaine、Glyceryl Stearate、Glycerin、Ceteareth-20、Cetyl Palmitate、 Glycine Soja(Soybean)Sterols、Phospholipids、Glycolipids、
FACIAL SCRUB INGREDIENT:

Aqua、 Coffea Arabica (Coffee) Seed Powder、Theobroma Cacao (Cocoa) Seed Butter、Butyrospermum Parkii (Shea) Butter、Tocopherol、CarthamusTinctorius (Safflower)Seed Oil、Glyceryl Stearate、 C15-19 Alkane、(Soybean) Sterols.Phospholipids、Glycolipids、Hydroxypropyl StarchPhosphate、Glycine Soja (Soybean) 0il、Crosspolymer.

Purpose section

Clean the skin surface.lmmediately smooth skin after use.Helps skin become brighter smoother and even-toned.

Warning

Avoid use on wounds or allergies

Massage gently to avoid irritating skin.

stop use

This product may cause allergic reactions in asmall number of people.
lf you experience any discomfort,please stop using it immediately.

not use

Not suitable for use by children, pregnantor breast feeding people.

OUT OF CHILDREN

KEEP THE PRODUCT OUT OF REACH OF CHILDREN to

HOW TO USE

Apply a generous amount of product onto wet skin.
Massagegently from neck to feet, then rinse with water.
Use 2-3 timesa week to achieve results.

Dosage

take an appropriateamount,Use 2-3 times a week